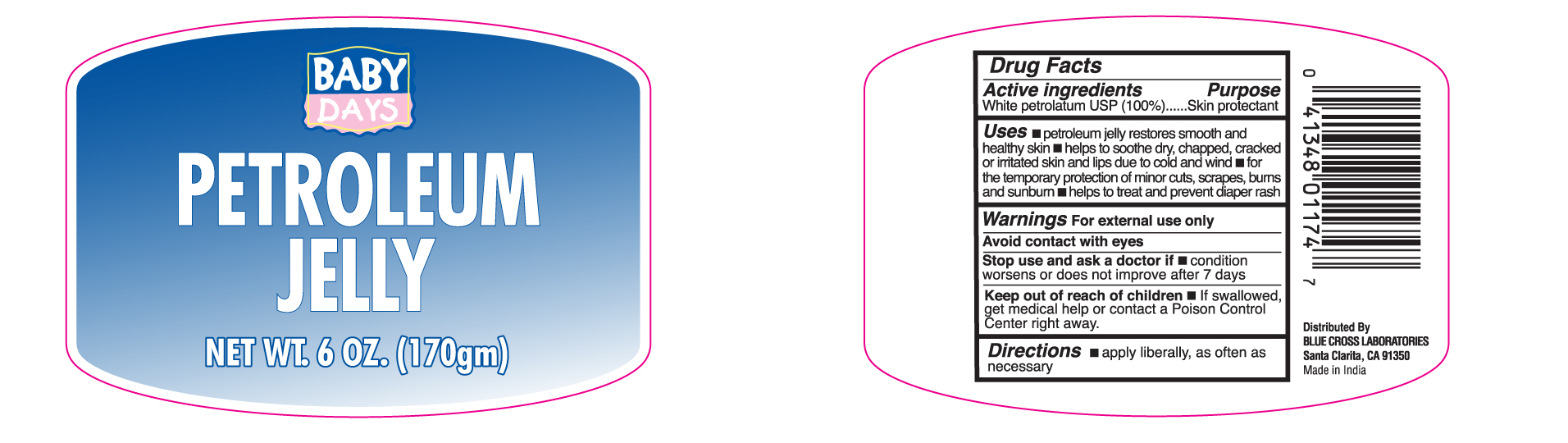 DRUG LABEL: Petroleum Jelly

NDC: 22431-133 | Form: JELLY
Manufacturer: Blue Cross Laboratories, Inc.
Category: otc | Type: HUMAN OTC DRUG LABEL
Date: 20201113

ACTIVE INGREDIENTS: PETROLATUM 100 g/100 g

Baby Days Petroleum Jelly

Active ingredients Purpose

White Petrolatum USP(100%) Skin Protectant

Uses

- Petroleum Jelly Restores smooth and healthy skin

- Helps to soothe dry, chapped, cracked, or irritated skin and lips due to cold and wind

- for the temporary protection protection of minor cuts, scrapes, burn and sunburn

- helps to treat and prevent diaper rash

Keep out of reach of children.

If swallowed, get medical help or contact a Poison Control Center right away.

Stop use and ask a doctor if condition worsens or does not improve after 7 days

Warnings

For external use only

Avoid contact with eyes

Directions

apply liberally, as often as necessary

INACTIVE INGREDIENT

None

PACKAGE LABEL

Baby Days

Petroleum Jelly

Net Wt. 6 oz. (170gm)